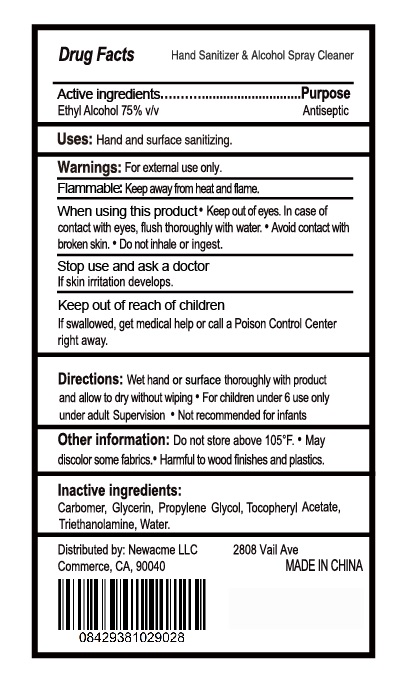 DRUG LABEL: Hand Sanitizer Alcohol Cleaner
NDC: 77753-001 | Form: SPRAY
Manufacturer: SHANDISHI Biological Technology Co., Ltd.
Category: otc | Type: HUMAN OTC DRUG LABEL
Date: 20200516

ACTIVE INGREDIENTS: ALCOHOL 75 mL/100 mL
INACTIVE INGREDIENTS: PROPYLENE GLYCOL; WATER; GLYCERIN; ALPHA-TOCOPHEROL ACETATE; CARBOXYPOLYMETHYLENE; TROLAMINE

77753-001 Hand Sanitizer Alcohol Spray Cleaner

Active Ingredient

Ethyl Alcohol 75%

Purpose

Antiseptic

Use

Hand and surface sanitizing.

WARNINGS

■For external use only
Flammable. Keep away from fire or flame
When using this product
n Keep out of eyes. In case of contact with eyes
flush thoroughly with water
■Avoid contact with open skin
1 Do not inhale or ingest
Stop use and ask a doctor
If skin iritation or redness develops

Keep out of reach of children
If swallowed , get medical help or contact a Poison Control Center right away

Directions

Wet hands thoroughly with product and allow to dry without wiping

Children under 6 years of age use only under adult supervision.

Not recommended for infants

Inactive ingredients

Carbomer, Glycerin, Propylene Glycol, Tocopheryl Acetate,
Triethanolamine, Water.